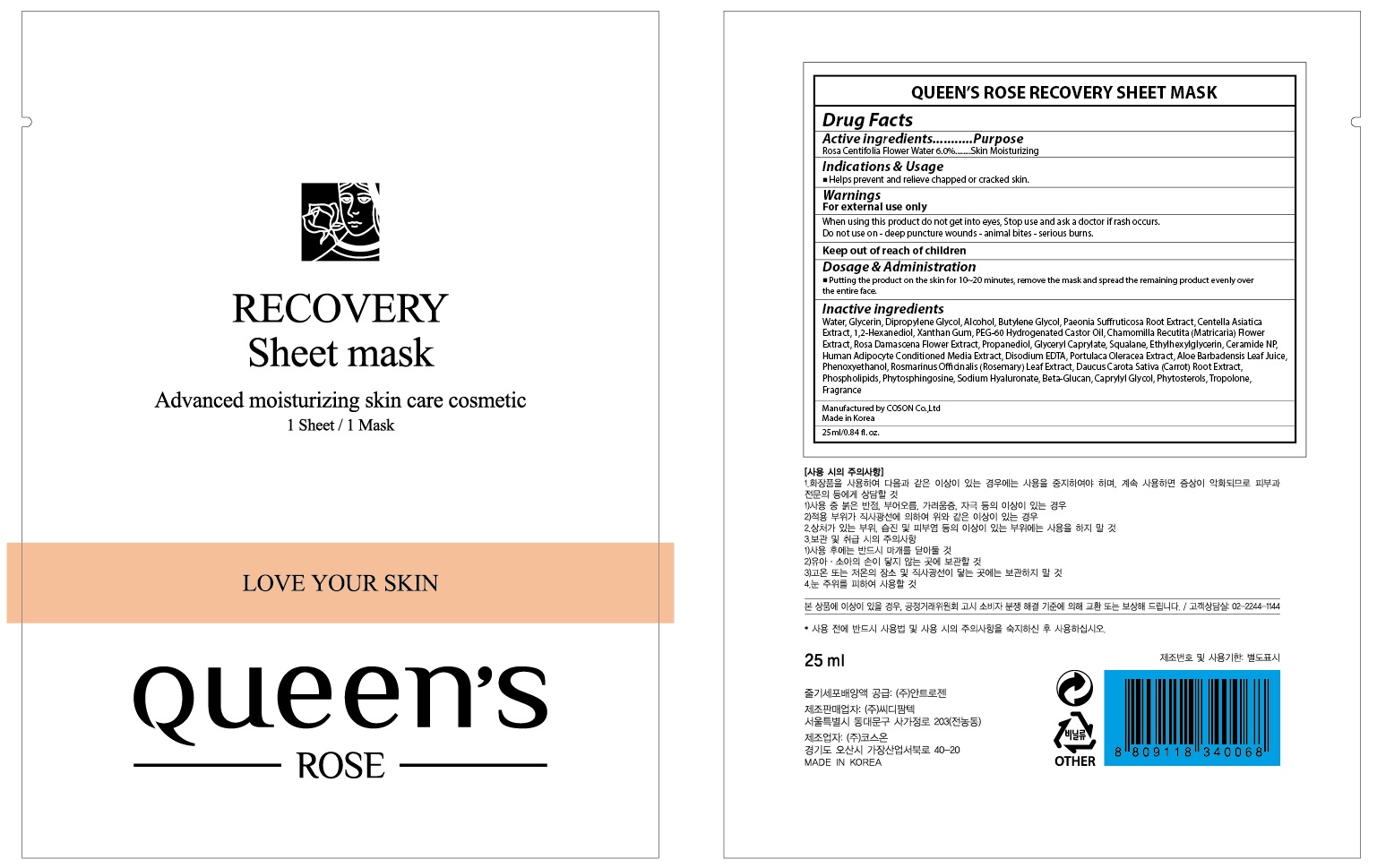 DRUG LABEL: QUEENS ROSE RECOVERY SHEET MASK
NDC: 71252-060 | Form: PATCH
Manufacturer: Cdpharmtec Co.,ltd
Category: otc | Type: HUMAN OTC DRUG LABEL
Date: 20170324

ACTIVE INGREDIENTS: ROSA CENTIFOLIA FLOWER OIL 1.5 g/25 mL
INACTIVE INGREDIENTS: Water; Glycerin

ACTIVE INGREDIENT

Active ingredients: Rosa Centifolia Flower Water 6.0%

INACTIVE INGREDIENT

Inactive ingredients: Water, Glycerin, Dipropylene Glycol, Alcohol, Butylene Glycol, Paeonia Suffruticosa Root Extract, Centella Asiatica Extract, 1,2-Hexanediol, Xanthan Gum, PEG-60 Hydrogenated Castor Oil, Chamomilla Recutita (Matricaria) Flower Extract, Rosa Damascena Flower Extract, Propanediol, Glyceryl Caprylate, Squalane, Ethylhexylglycerin, Ceramide NP, Human Adipocyte Conditioned Media Extract, Disodium EDTA, Portulaca Oleracea Extract, Aloe Barbadensis Leaf Juice, Phenoxyethanol, Rosmarinus Officinalis (Rosemary) Leaf Extract, Daucus Carota Sativa (Carrot) Root Extract, Phospholipids, Phytosphingosine, Sodium Hyaluronate, Beta-Glucan, Caprylyl Glycol, Phytosterols, Tropolone, Fragrance

PURPOSE

Purpose: Skin Moisturizing

WARNINGS

Warnings: For external use only When using this product do not get into eyes, Stop use and ask a doctor if rash occurs. Do not use on - deep puncture wounds - animal bites - serious burns.

KEEP OUT OF REACH OF CHILDREN

INDICATIONS & USAGE

Indications & Usage: Helps prevent and relieve chapped or cracked skin.

DOSAGE & ADMINISTRATION

Dosage & Administration: - Take a proper amount of product, and spread it evenly over the entire face. - Apply in daily skin care routine.